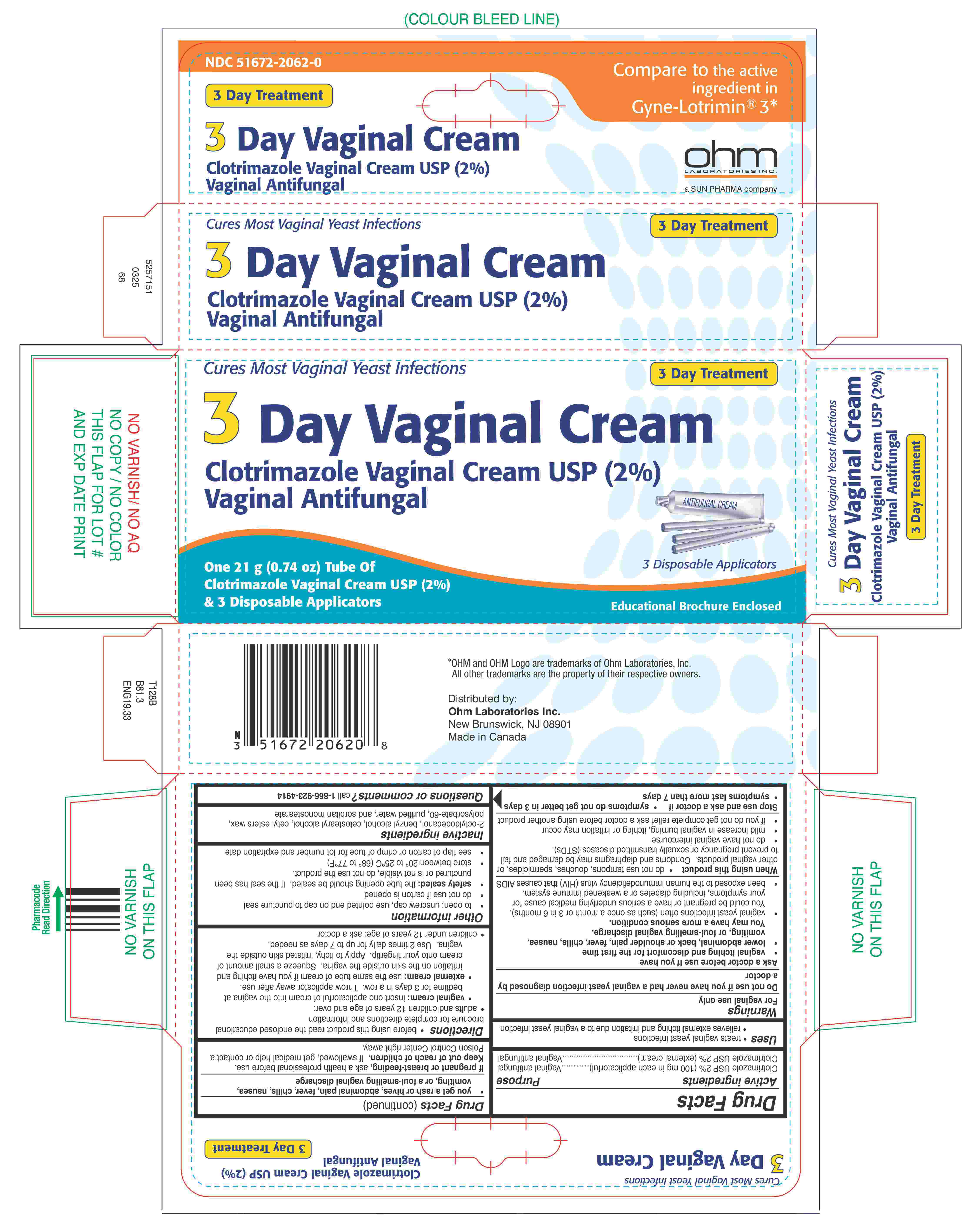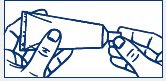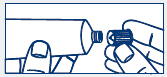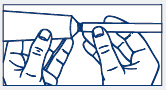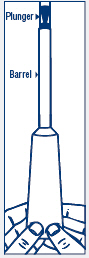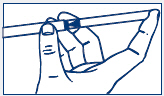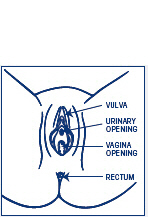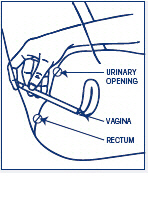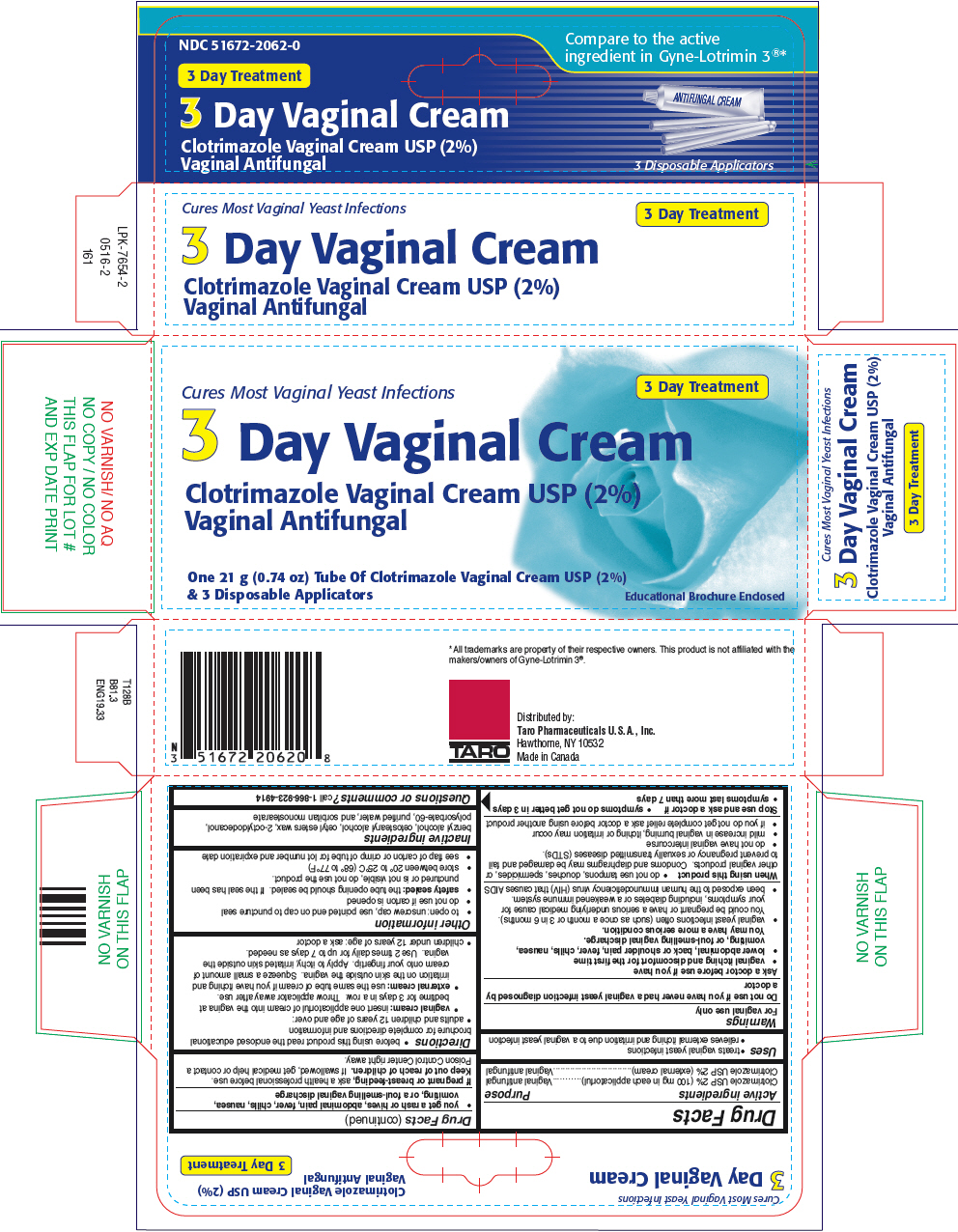 DRUG LABEL: Clotrimazole
NDC: 51672-2062 | Form: CREAM
Manufacturer: Sun Pharmaceutical Industries, Inc.
Category: otc | Type: HUMAN OTC DRUG LABEL
Date: 20250702

ACTIVE INGREDIENTS: CLOTRIMAZOLE 2 g/100 g
INACTIVE INGREDIENTS: BENZYL ALCOHOL; CETOSTEARYL ALCOHOL; CETYL ESTERS WAX; OCTYLDODECANOL; POLYSORBATE 60; WATER; SORBITAN MONOSTEARATE

Clotrimazole

Drug Facts

ACTIVE INGREDIENT

Active ingredients | Purpose
Clotrimazole USP 2% (100 mg in each applicatorful) | Vaginal Antifungal
Clotrimazole USP 2% (external cream) | Vaginal Antifungal

Use

- treats vaginal yeast infections
- relieves external itching and irritation due to a vaginal yeast infection

Warnings

For vaginal use only

Do not use if you have never had a vaginal yeast infection diagnosed by a doctor

Ask a doctor before use if you have

- vaginal itching and discomfort for the first time
- lower abdominal, back or shoulder pain, fever, chills, nausea, vomiting, or foul-smelling vaginal discharge. You may have a more serious condition.
- vaginal yeast infections often (such as once a month or 3 in 6 months). You could be pregnant or have a serious underlying medical cause for your symptoms, including diabetes or a weakened immune system.
- been exposed to the human immunodeficiency virus (HIV) that causes AIDS

When using this product

- do not use tampons, douches, spermicides, or other vaginal products. Condoms and diaphragms may be damaged and fail to prevent pregnancy or sexually transmitted diseases (STDs).
- do not have vaginal intercourse
- mild increase in vaginal burning, itching or irritation may occur
- if you do not get complete relief ask a doctor before using another product

Stop use and ask a doctor if

- symptoms do not get better in 3 days
- symptoms last more than 7 days
- you get a rash or hives, abdominal pain, fever, chills, nausea, vomiting, or a foul-smelling vaginal discharge

PREGNANCY OR BREAST FEEDING

If pregnant or breast-feeding,ask a health professional before use.

Keep out of reach of children.If swallowed, get medical help or contact a Poison Control Center right away.

Directions

- before using this product read the enclosed educational brochure for complete directions and information
- adults and children 12 years of age and over:
  - vaginal cream:insert one applicatorful of cream into the vagina at bedtime for 3 days in a row. Throw applicator away after use.
  - external cream:use the same tube of cream if you have itching and irritation on the skin outside the vagina. Squeeze a small amount of cream onto your fingertip. Apply to itchy, irritated skin outside the vagina. Use 2 times daily for up to 7 days as needed.
- children under 12 years of age: ask a doctor

Other information

- To open: unscrew cap, use pointed end on cap to puncture seal
- do not use if carton is opened
- safety sealed:the tube opening should be sealed. If the seal has been punctured or is not visible, do not use the product.
- store between 20° to 25°C (68° to 77°F)
- see flap of carton or crimp of tube for lot number and expiration date

Inactive ingredients

2-octyldodecanol, benzyl alcohol, cetostearyl alcohol, cetyl esters wax, polysorbate-60, purified water, and sorbitan monostearate

Questions or comments?

call 1-866-923-4914

Distributed by:

Ohm Laboratories Inc.
New Brunswick, NJ 08901
Made in Canada

EDUCATIONAL BROCHURE

Read This Before Using
Clotrimazole Vaginal Cream USP (2%)
Vaginal Antifungal

Clotrimazole USP 2% (100 mg in each applicatorful).

3-day treatment of vaginal yeast infections.

Uses:

- For the treatment of vaginal yeast infections.
- Relieves external itching and irritation due to a vaginal yeast infection.

If you have symptoms such as vaginal itching, burning, or discharge, and if at some time in the past your doctor has told you that these symptoms were due to a vaginal yeast infection, then Clotrimazole Vaginal Cream should work for you. If, however, you have never had these symptoms or a vaginal yeast infection before, you should see your doctor before using this product.

What is a Vaginal Yeast Infection?

A yeast infection is a common type of vaginal infection. Your doctor may call it candidiasis. This condition is caused by an organism called Candida, which is a type of yeast. Healthy women usually have this yeast on the skin, in the mouth, in the digestive tract, and in the vagina. At times, the yeast can grow very quickly. In fact, the infection is sometimes called yeast (Candida)"overgrowth." Some women may have a yeast infection on the skin outside the vagina (vulva) associated with the vaginal infection.

A yeast infection can occur at any age. It is most common during the childbearing years. Women who are pregnant or diabetic, taking antibiotics, birth control pills or steroids, or who have a weakened immune system are more likely to get repeated yeast infections.

Various medical conditions can damage the body's normal defenses against infection.

One of the most serious of these conditions is infection with the human immuno-deficiency virus (HIV-the virus that causes AIDS). The HIV virus causes the body to be more likely to get infections, including vaginal yeast infections. Therefore, women with HIV infection may have frequent vaginal yeast infections that do not clear up easily with proper treatment. If you may have been exposed to HIV and are experiencing repeated vaginal yeast infections, you should see your doctor right away. For additional information on HIV infection, please contact your doctor or the CDC National AIDS HOT-LINE. The CDC phone numbers are: 1-800-CDC-INFO (1-800-232-4636) for English or Spanish or 1-888-232-6348 (hearing impaired, TDD/TTY).

Symptoms of a Vaginal Yeast Infection

There are many symptoms of a vaginal yeast infection. They can include:

- Vaginal itching (ranging from mild to severe).
- A clumpy, vaginal discharge that may look like cottage cheese.
- Vaginal soreness, irritation, or burning.
- Rash or redness on the skin outside the vagina (vulvar irritation).

Note:Vaginal discharge that is different from above, for example, a yellow/green discharge or a foul-smelling discharge may mean that you have a different infection. If this is the case, you should talk to your doctor before using Clotrimazole Vaginal Cream.

For Best Results

1. Be sure to use this product for the full 3 days, even if your symptoms go away sooner.

2. Use one applicatorful of Clotrimazole Vaginal Cream at bedtime for three days in a row, even during your menstrual period.

3. Wear cotton underwear.

4. If your partner has itching, redness or discomfort of his penis, he should consult his doctor. He should tell the doctor that you are treating yourself for a vaginal yeast infection.

5. Dry the outside vaginal area thoroughly after a shower, bath or swim. Change out of a wet bathing suit or damp clothes as soon as possible. A dry area is less likely to lead to the growth of yeast.

6. Wipe from front to rear after a bowel movement or urination.

7. Do not douche unless your doctor tells you to do so. Douching may wash the product out of the vagina.

8. Try not to scratch the skin outside the vagina. Scratching can cause more irritation and can spread the infection.

9. Discuss with your doctor any drugs you are now taking. You are more likely to get a vaginal yeast infection with certain drugs.

10. Do not have vaginal intercourse while using this product.

11. When using this product, condoms and diaphragms may be damaged and fail to prevent pregnancy or sexually transmitted diseases (STDs).

If you have a Question

Questions of a medical nature should be taken up with your doctor. If you have any other questions or need information on this product call toll free 1-866-923-4914.

Active Ingredient:

Clotrimazole USP, 2% (100 mg in each applicatorful)

Clotrimazole USP, 2% (external cream)

Inactive Ingredients:

Benzyl alcohol, cetostearyl alcohol, cetyl esters wax, 2-octyldodecanol, polysorbate 60, purified water, sorbitan monostearate.

Storage

Store between 20° to 25°C (68° to 77°F).

See end panel of carton and end of tube for lot number and expiration date.

Warnings

For vaginal use only.

Do not use if you have never had a vaginal yeast infection diagnosed by a doctor.

Ask a doctor before use if you have

- vaginal itching and discomfort for the first time
- lower abdominal, back or shoulder pain, fever, chills, nausea, vomiting or foul-smelling vaginal discharge. You may have a more serious condition.
- vaginal yeast infections often (such as once a month or 3 in 6 months). You could be pregnant or have a serious underlying medical cause for your symptoms, including diabetes or a weakened immune system.
- been exposed to the human immunodeficiency virus (HIV) that causes AIDS

When using this product

- do not use tampons, douches, spermicides or other vaginal products. Condoms and diaphragms may be damaged and fail to prevent pregnancy or sexually transmitted diseases (STDs).
- do not have vaginal intercourse
- mild increase in vaginal burning, itching or irritation may occur
- if you do not get complete relief, ask a doctor before using another product

Stop use and ask a doctor if

- symptoms do not get better in 3 days
- symptoms last more than 7 days
- you get a rash or hives, abdominal pain, fever, chills, nausea, vomiting or foul-smelling vaginal discharge

If pregnant or breast-feeding,ask a health professional before use.

Keep out of reach of children.If swallowed, get medical help or contact a Poison Control Center right away.

Safety sealed:the tube opening should be sealed. If the seal has been punctured or is not visible, do not use the product.

How to use Clotrimazole Vaginal Cream with 3 Disposable Applicators

Directions for Use

Use the cream at bedtime for 3 days in a row.

Read the full directions below before using.

1. To open the tube, unscrew the cap.

Press the sharp point of the cap into the sealed end of the tube. Push down firmly until the seal is broken. (see picture)

2. Attach the applicator to the tube of cream by placing end of the applicator firmly onto tube of cream. (see picture)

3. Gently squeeze opposite end of tube, forcing cream into barrel of applicator. The plunger will stop moving outward when the barrel is full. Separate the applicator from the tube. After each use, replace cap and roll up the tube from the bottom.

4. Hold the barrel as shown in the picture.

5. The Clotrimazole Vaginal Cream applicator is inserted into the vagina in much the same way as a tampon. Gently insert the applicator into the vagina as far back as it will go comfortably. This can be done while lying on your back with your knees bent (as shown in the picture), or while standing with your feet apart and your knees bent.

6. With one hand holding the barrel, use the other hand to push the plunger into the barrel as far as it will go. Remove the applicator from the vagina.

7. Throw the applicator away after each use. Do not flush down the toilet.

8. Lie down as soon as possible to keep the cream from leaking out.

9. Repeat steps 2 through 8 before bedtime for the next 2 days.

To protect your clothing from leakage or discharge, you may want to use deodorant-free pads or panty shields while you are using Clotrimazole Vaginal Cream. Do not use tampons, douches, or spermicides or other vaginal productsuntil after you have completed the treatment and your symptoms are gone.

Distributed by:
Ohm Laboratories Inc.
New Brunswick, NJ 08901
Made in Canada
5257152 0125 161

PRINCIPAL DISPLAY PANEL - 21 g Tube Carton

Cures Most Vaginal Yeast Infections

3 Day Treatment

3 Day Vaginal Cream

Clotrimazole Vaginal Cream USP (2%)
Vaginal Antifungal

One 21 g (0.74 oz) Tube Of Clotrimazole Vaginal Cream USP (2%)
& 3 Disposable Applicators

Educational Brochure Enclosed